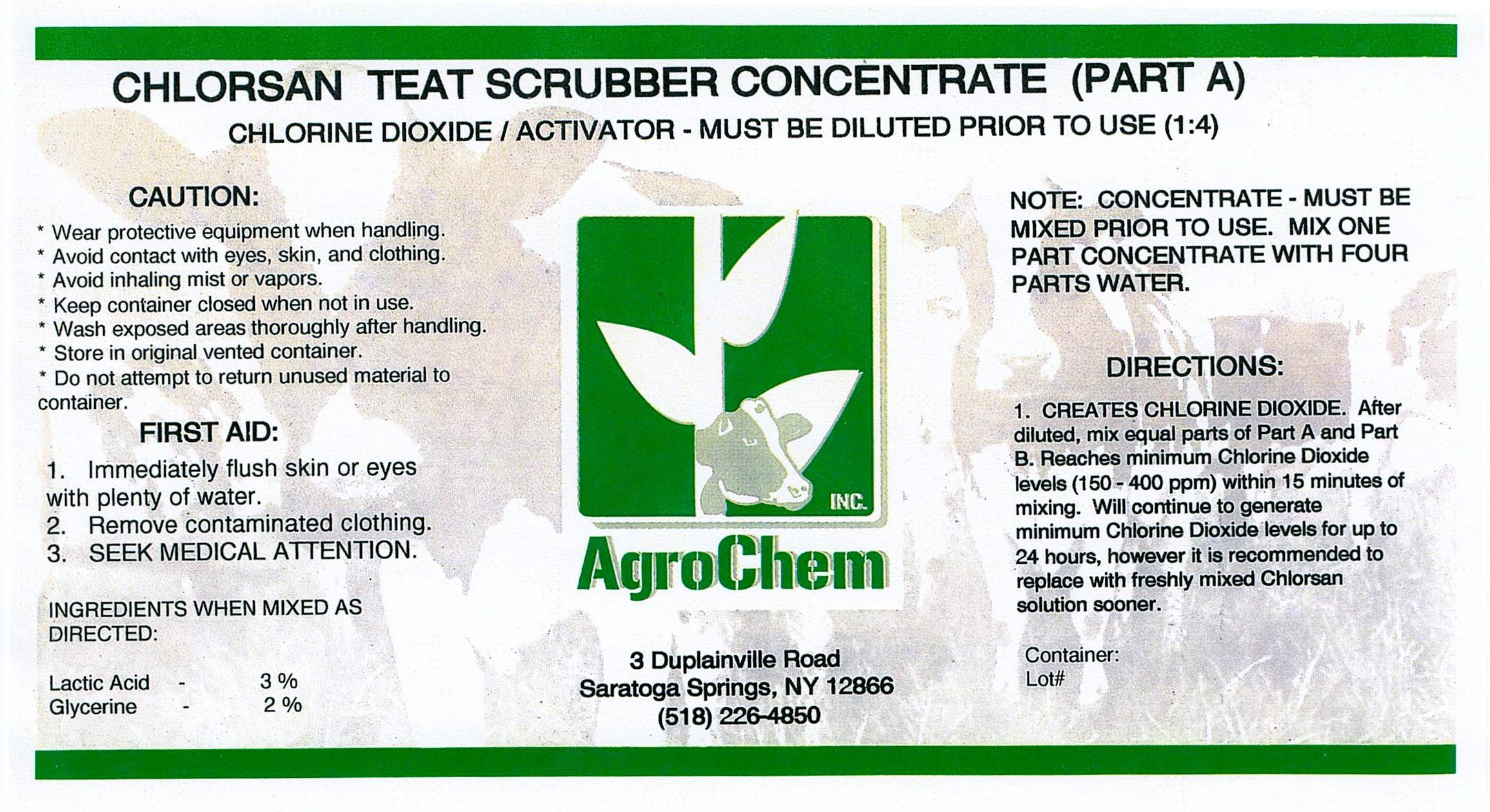 DRUG LABEL: Chlorsan Teat Scrubber Concentrate Part A
NDC: 17307-3656 | Form: SOLUTION
Manufacturer: AgroChem Inc
Category: animal | Type: OTC ANIMAL DRUG LABEL
Date: 20131030

ACTIVE INGREDIENTS: LACTIC ACID 0.03 kg/1 kg
INACTIVE INGREDIENTS: GLYCERIN 0.02 kg/1 kg; DODECYLBENZENESULFONIC ACID 0.02 kg/1 kg; ALCOHOL 0.004 kg/1 kg

Chlorsan Teat Scrubber Concentrate Part A

DESCRIPTION

CHLORINE DIOXIDE/ACTIVATOR - MUST BE DILUTED PRIOR TO USE (1:4)

WARNINGS AND PRECAUTIONS

CAUTION:

* Wear protective equipment when handling.

* Avoid contact with eyes, skin, and clothing.

* Avoid inhaling mist or vapors.

* Keep container closed when not in use.

* Wash exposed area thoroughly after handling.

* Store in original vented container.

* Do not attempt to return unused material to

container.

FIRST AID:

1. Immediately flush skin or eyes with

plenty of water.

2. Remove contaminated clothing.

3. SEEK MEDICAL ATTENTION.

ACTIVE INGREDIENT

INGREDIENTS WHEN MIXED AS

DIRECTED:

Lactic Acid - 3%

Glycerine - 2%

INSTRUCTIONS FOR USE

NOTE: CONCENTRATE - MUST BE

MIXED PRIOR TO USE. MIX ONE

PART CONCENTRATE WITH FOUR

PARTS WATER.

DIRECTIONS:

1. CREATES CHLORINE DIOXIDE. After

diluted mix equal parts of Part A and

Part B. Reaches minimum Chlorine

Dioxide levels (150 - 400 ppm) within 15

minutes of mixing. Will continue to

generate minimum Chlorine Dioxide

levels for up to 24 hours, however it is

recommended to replace with freshly

mixed Chlorsan solution sooner.